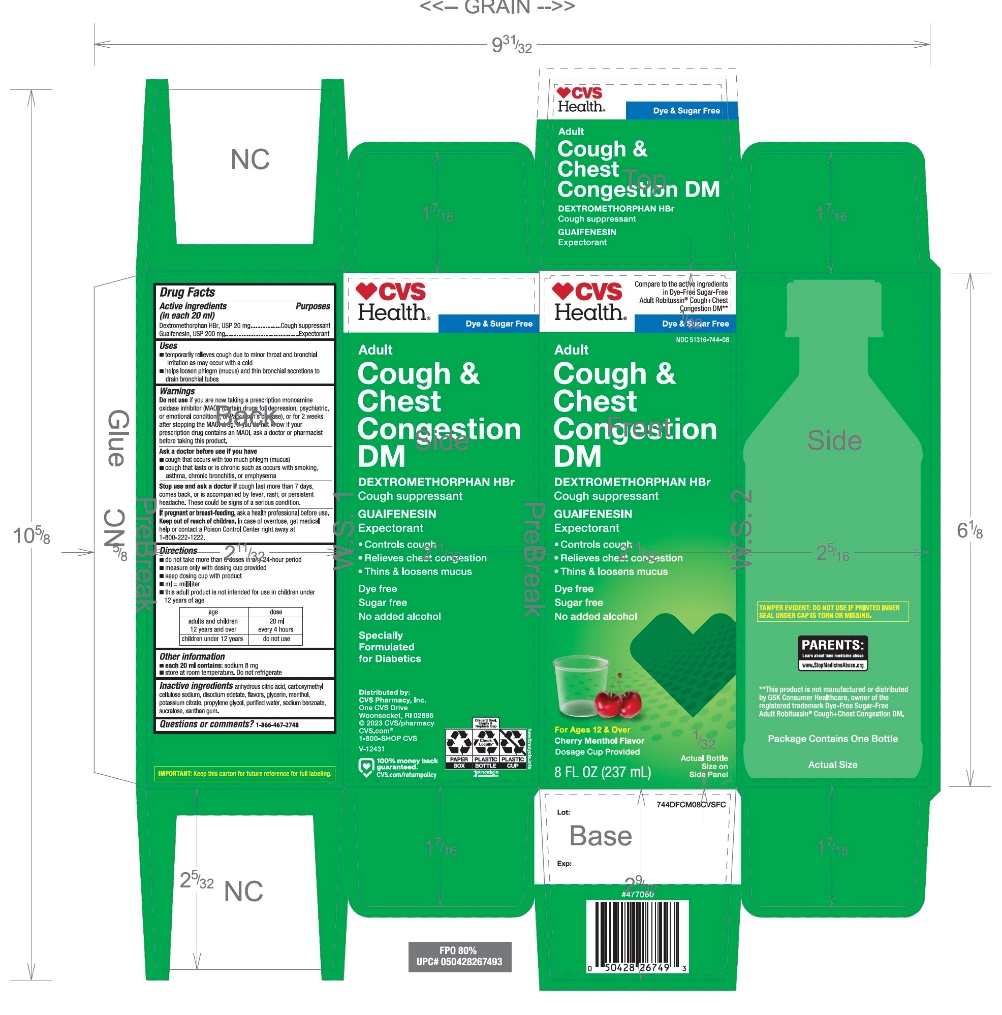 DRUG LABEL: CVS ADULT COUGH PLUS CHEST CONGESTION DM
NDC: 51316-744 | Form: SOLUTION
Manufacturer: CVS PHARMACY
Category: otc | Type: HUMAN OTC DRUG LABEL
Date: 20251210

ACTIVE INGREDIENTS: DEXTROMETHORPHAN HYDROBROMIDE 20 mg/20 mL; GUAIFENESIN 200 mg/20 mL
INACTIVE INGREDIENTS: ANHYDROUS CITRIC ACID; CARBOXYMETHYLCELLULOSE SODIUM, UNSPECIFIED; EDETATE DISODIUM; GLYCERIN; MENTHOL, UNSPECIFIED FORM; POTASSIUM CITRATE; PROPYLENE GLYCOL; WATER; SODIUM BENZOATE; SUCRALOSE; XANTHAN GUM

CVS Adult Cough+Chest Congestion DM Drug Facts

Active ingredients (in each 20 ml)

Dextromethorphan HBr, USP 20 mg

Guaifenesin, USP 200 mg

Purposes

Cough suppressant

Expectorant

Uses

- temporarily relieves cough due to minor throat and bronchial irritation as may occur with a cold
- helps loosen phlegm (mucus) and thin bronchial secretions to drain bronchial tubes

Warnings

DO NOT USE

Do not useif you are now taking a prescription monoamine oxidase inhibitor (MAOI) (certain drugs for depression, psychiatric, or emotional conditions, or Parkinson's disease), or for 2 weeks after stopping the MAOI drug. If you do not know if your prescription drug contains an MAOI, ask a doctor or pharmacist before taking this product.

Ask a doctor before use if you have

- cough that occurs with too much phlegm (mucus)
- cough that lasts or is chronic such as occurs with smoking, asthma, chronic bronchitis, or emphysema

Stop use and ask a doctor ifcough lasts more than 7 days, comes back, or is accompanied by fever, rash, or persistent headache. These could be signs of a serious condition.

PREGNANCY OR BREAST FEEDING

If pregnant or breast-feeding,ask a health professional before use.

Keep out of reach of children.In case of overdose, get medical help or contact a Poison Control Center right away at 1-800-222-1222.

Directions

- do not take more than 6 doses in any 24-hour period
- measure only with dosing cup provided
- keep dosing cup with product
- ml = milliliter
- this adult product is not intended for use in children under 12 years of age

age | dose
adults and children 12 years and over | 20 ml every 4 hours
children under 12 years | do not use

Other information

- each 20 ml contains:sodium 8 mg
- store at room temperature. Do not refrigerate.

Inactive ingredients

anhydrous citric acid, carboxymethyl cellulose sodium, disodium edetate, flavors, glycerin, potassium citrate, propylene glycol, purified water, sodium benzoate, sucralose, xanthan gum

Questions or comments?

1-866-467-2748

PRINCIPAL DISPLAY PANEL

Compare to the active ingredients in Dye-Free Sugar-Free Adult Robitussin Cough + Chest Congestion DM*
NDC 51316-744-08
DYE-FREE

Adult

Cough+Chest
Congestion DM

Dextromethorphan HBr (Cough Suppressant)
Guaifenesin (Expectorant)

- Controls Cough
- Relieves Chest Congestion
- Thins & Loosens Mucus

Sugar-Free

No Added Alcohol
Specially
Formulated
for DIABETICS
Cherry Menthol Flavor

For Ages 12 & Over
8 FL OZ (237 ml)

*This product is not manufactured or distributed by GSK Consumer Healthcare, owner of the registered trademark DYE-FREE Sugar-Free Adult Robitussin Cough+chest Congestion DM.